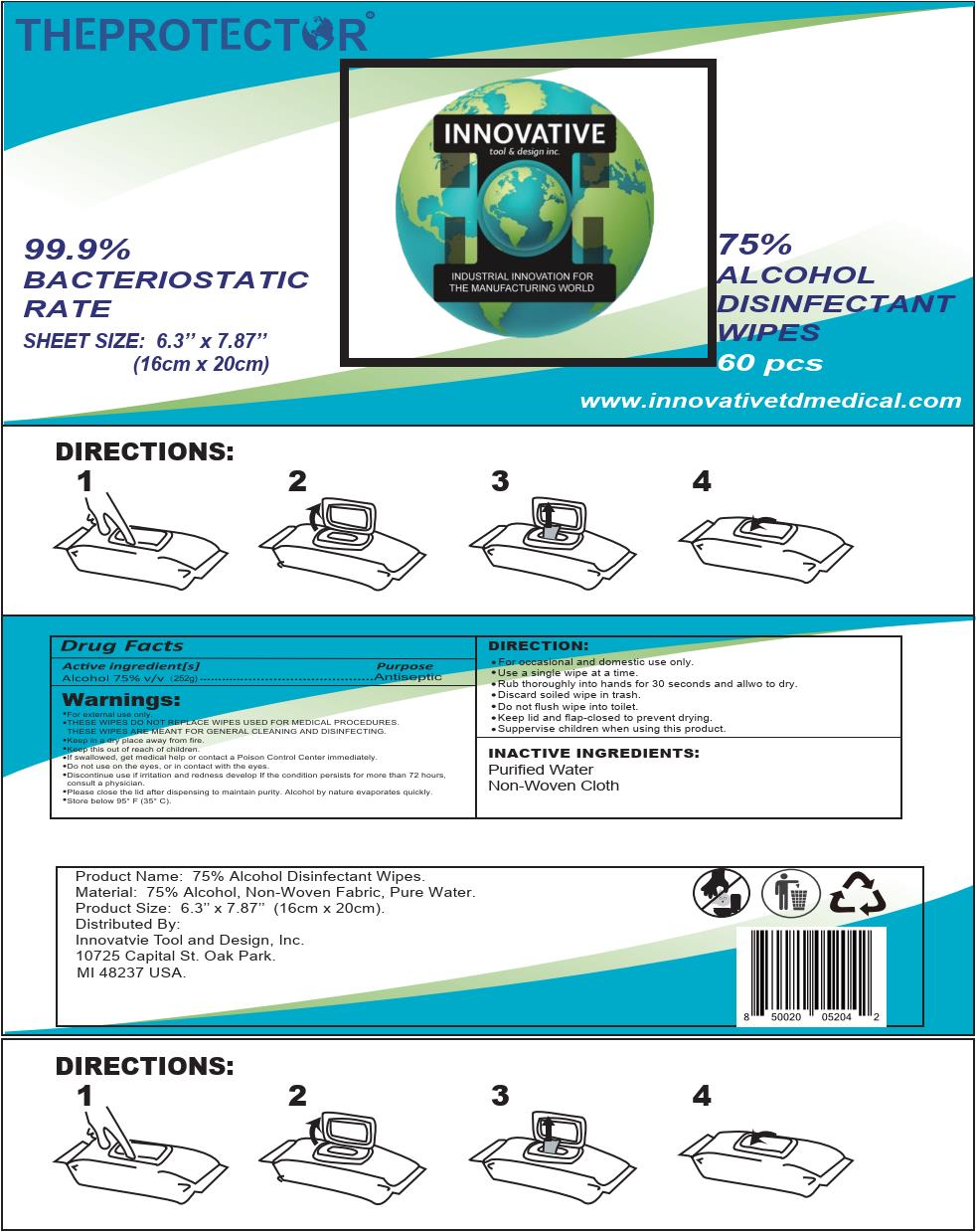 DRUG LABEL: Wet Wipes
NDC: 79014-011 | Form: CLOTH
Manufacturer: Wenzhou Bofeng Medical and Sanitary Products Co., Ltd.
Category: otc | Type: HUMAN OTC DRUG LABEL
Date: 20220825

ACTIVE INGREDIENTS: ALCOHOL 3.75 mL/1 1
INACTIVE INGREDIENTS: WATER

Innovative Wipes, 75% Alcohol, 60pcs

Active Ingredient(s)

Alcohol 75% v/v. Purpose: Antiseptic

Purpose

Antiseptic

Use

For hand sanitizing to decrease bacteria on the skin.

Warnings

- For external use only.
- THESE WIPES DO NOT REPLACE WIPES USED FOR MEDICAL PROCEDURES.

THESE WIPES ARE MEANT FOR GENERAL CLEANING AND DISINFECTING.

- Keep in a dry place away from fire.
- Keep this out of reach of children.
- If swallowed, get medical help or contact a Poison Control Center immediately.
- Do not use on the eyes, or in contact with the eyes.
- Discontinue use if irritation and redness develop If the condition persists for more than 72 hours, consult a physician.
- Please close the lid after dispensing to maintain purity. Alcohol by nature evaporates quickly.
- Store below 95° F (35° C)

STOP USE

Discontinue use if irritation and redness develop If the condition persists for more than 72 hours, consult a physician.

Keep this out of reach of children.

Directions

- For occasional and domestic use only.
- Use a single wipe at a time.
- Rub thoroughly into hands for 30 seconds and allwo to dry.
- Discard soiled wipe in trash.
- Do not flush wipe into toilet.
- Keep lid and flap-closed to prevent drying.
- Suppervise children when using this product.

Inactive Ingredient(s)

Purified Water